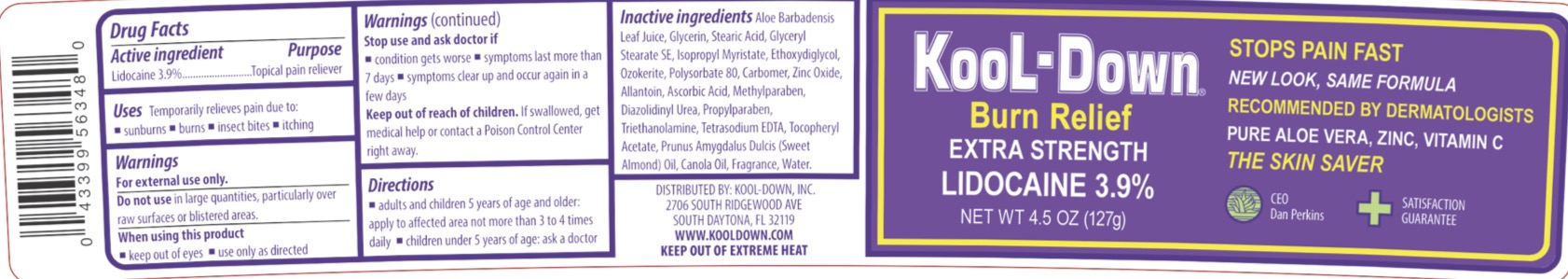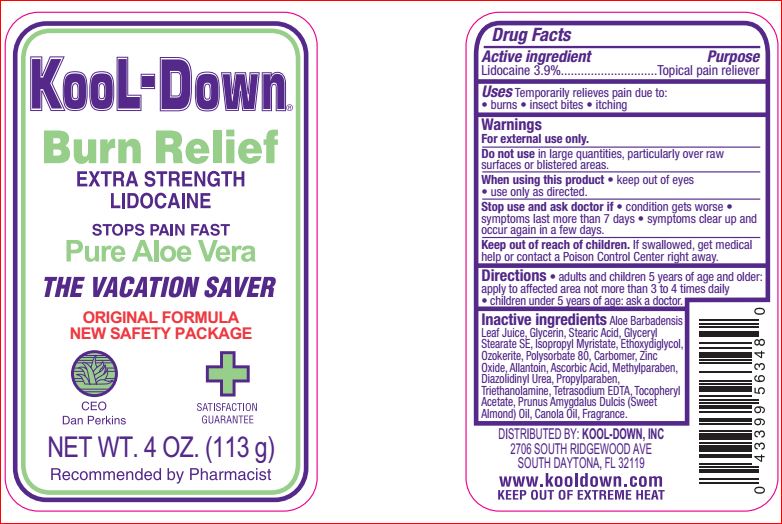 DRUG LABEL: Burn Relief Extra Strength
NDC: 61566-279 | Form: CREAM
Manufacturer: Kool-Down Inc
Category: otc | Type: HUMAN OTC DRUG LABEL
Date: 20250625

ACTIVE INGREDIENTS: LIDOCAINE 3.9 g/100 g
INACTIVE INGREDIENTS: ALOE; GLYCERIN; STEARIC ACID; GLYCERYL STEARATE SE; ISOPROPYL MYRISTATE; DIETHYLENE GLYCOL MONOETHYL ETHER; CERESIN; POLYSORBATE 80; CARBOXYPOLYMETHYLENE; ZINC OXIDE; ALLANTOIN; ASCORBIC ACID; METHYLPARABEN; DIAZOLIDINYL UREA; PROPYLPARABEN; TROLAMINE; EDETATE SODIUM; .ALPHA.-TOCOPHEROL ACETATE; ALMOND OIL; CANOLA OIL

Active ingredient

Lidocaine - 3.9%

Purpose

Topical Pain Reliever

Uses

Temporarily relieves pain due to:

- burns
- insect bites
- itching

Warnings

For external use only.

Do not use in large quantities, particularity over raw surfaces or blistered areas.

When using this product keep out of eyes, use only as directed.

Stop use and ask a doctor if condition worsens or symptoms last more than 7 days or clear up and occur again within a few days.

Keep Out of Reach of Children

If swallowed, get medical help or contact a Poison Control Center right away.

Directions

Adults and children 5 years of age and older: apply to affected area not more that 3-4 times daily. Children under 5 years of age: ask a doctor.

Inactive ingredients

Aloe Barbadensis Leaf Juice, Glycerin, Stearic Acid, Glyceryl Stearate SE, Isopropyl Myristate, Ethoxydiglycol, Ozokerite, Polysorbate 80, Carbomer, Zinc Oxide, Allantoin, Ascorbic Acid, Methylparaben, Diazolidinyl Urea, Propylparaben, Triethanolamine, Tetrasodium EDTA, Tocopheryl Acetate, Prunus Amygdalus Dulcis (Sweet Almond) Oil, Canola Oil, Fragrance.